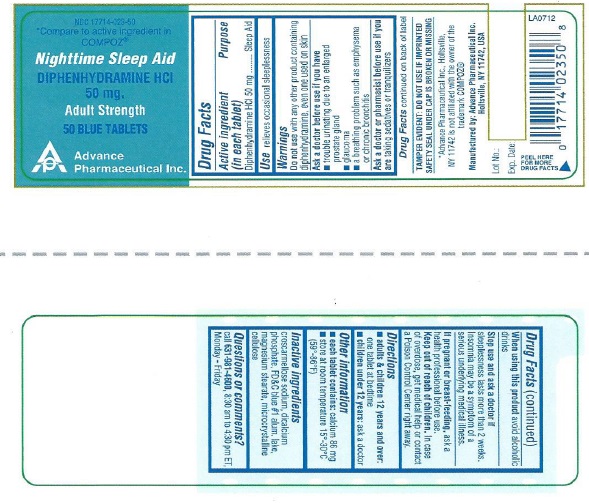 DRUG LABEL: Diphenhydramine Hydrochloride
NDC: 17714-023 | Form: TABLET
Manufacturer: Advance Pharmaceutical Inc.
Category: otc | Type: HUMAN OTC DRUG LABEL
Date: 20171030

ACTIVE INGREDIENTS: DIPHENHYDRAMINE HYDROCHLORIDE 50 mg/1 1
INACTIVE INGREDIENTS: CROSCARMELLOSE SODIUM; D&C YELLOW NO. 10; ANHYDROUS DIBASIC CALCIUM PHOSPHATE; MAGNESIUM STEARATE; MICROCRYSTALLINE CELLULOSE; SILICON DIOXIDE; STARCH, CORN

DIPHENHYDRAMINE HYDROCHLORIDE TABLETS, USP 50mg

Active Ingredient

(in each TABLET)

Diphenhydramine HCl 50 mg

Purpose

Sleep Aid

Uses

relieves occasional sleeplessness

Warnings

Do not use with any other product containing diphenhydramine, even one used on skin

Ask a doctor before use if you have

- glaucoma
- trouble urinating due to an enlarged prostate gland
- a breathing problem such as emphysema or chronic bronchitis
  Ask a doctor or pharmacist before use if you are taking sedatives or tranquilizers
  When using this product
- you may get very drowsy
- avoid alcoholic drinks
- alcohol, sedatives & tranquilizers may increase drowsiness
- be careful when driving a motor vehicle or operating machinery
- excitability may occur, especially in children
  If pregnant or breast-feeding, ask a health professional before use.

Keep out of reach of children.

In case of overdose, get medical help or contact a Poison Control Center right away.

Directions

- adults and children 12 years and over: take 1 tablet at bedtime
- children under 12 years: ask a doctor

Other Information

- store at 15-30 °C (59-86 °F)
- protect from moisture

Inactive Ingredients

Croscarmellose sodium, dicalcium phosphate, FD&amp;C blue# 1(Al-lake), Magnesium stearate, microcrystalline cellulose.

Questions or Comments

TAMPER EVIDENT: DO NOT USE IF IMPRINTED SAFETY SEAL UNDER CAP OR BAND AROUND ANY CAPSULE IS MISSING OR DAMAGED

Manufactured by: Advance Pharmaceutical Inc. Holtsville, NY 11742

Call 631-981-4600, 8:30 am to 4:30 pm ET, Monday-Friday

PACKAGE LABEL.PRINCIPAL DISPLAY PANEL

DIPHENHYDRAMINE HYDROCHLORIDE Tablet, USP 50 MG

ANTIHISTAMINE

NDC: 17714-023-50 – 50 COUNT